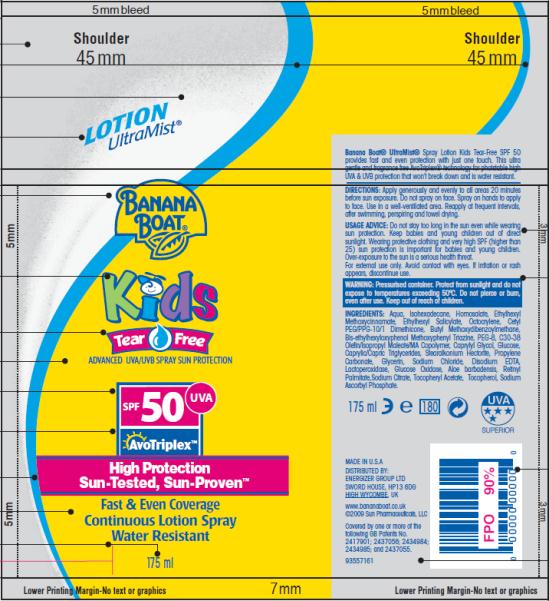 DRUG LABEL: Banana Boat UltraMist Kids Tear Free Lotion SPF 50
NDC: 17630-2007 | Form: SPRAY
Manufacturer: Accra-Pac, Inc.
Category: otc | Type: HUMAN OTC DRUG LABEL
Date: 20100321

ACTIVE INGREDIENTS: HOMOSALATE 0.1 mL/1 mL; OCTINOXATE 0.075 mL/1 mL; OCTISALATE 0.05 mL/1 mL; OCTOCRYLENE 0.05 mL/1 mL; AVOBENZONE 0.03 mL/1 mL
INACTIVE INGREDIENTS: BEMOTRIZINOL; CAPRYLYL GLYCOL; MEDIUM-CHAIN TRIGLYCERIDES; PROPYLENE CARBONATE; GLYCERIN; SODIUM CHLORIDE; EDETATE DISODIUM; GLUCOSE OXIDASE; VITAMIN A PALMITATE; SODIUM CITRATE; .ALPHA.-TOCOPHEROL ACETATE, D-; SODIUM ASCORBYL PHOSPHATE

Banana Boat UltraMist Kids Tear Free Lotion Spray SPF 50

ACTIVE INGREDIENTS:

Homosalate 0.1mL / 1mL

Octinoxate 0.075mL / 1mL

Octisalate 0.05mL / 1mL

Octocrylene 0.05mL / 1mL

Avobenzone 0.03mL / 1mL

DIRECTIONS:

Apply generously and evenly to all areas 20 minutes before sun exposure. Do not spray on face. Spray on hands to apply to face. Use in a well-ventilated area. Reapply at frequent intervals, after swimming, perspiring and towel drying.

USAGE ADVICE:

Do not stay too long in the sun even while wearing sun protection. Keep babies and young children out of direct sunlight. Wearing protective clothing and very high SPF (higher than 25) sun protection is important for babies and young children. Over-exposure to the sun is a serious health threat. For external use only. Avoid contact with eyes. If irritation or rash appears, discontinue use.

WARNING:

Pressurised container. Protect from sunlight and do not expose to temperatures exceeding 50ºC. Do not pierce or burn, even after use. Keep out of reach of children.

INGREDIENTS:

Aqua, Isohexadecane, Homosalate, Ethylhexyl Methoxycinnamate, Ethylhexyl Salicylate, Octocrylene, Cetyl PEG/PPG-10/1 Dimethicone, Butyl Methoxydibenzoylmethane, Bis-ethylhexyloxyphenol Methoxyphenyl Triazine, PEG-8, C30-38 Olefin/Isopropyl Maleate/MA Copolymer, Caprylyl Glycol, Glucose, Caprylic/Capric Triglycerides, Stearalkonium Hectorite, Propylene Carbonate, Glycerin, Sodium Chloride, Disodium EDTA, Lactoperoxidase, Glucose Oxidase, Aloe barbadensis, Retinyl Palmitate,Sodium Citrate, Tocopheryl Acetate, Tocopherol, Sodium Ascorbyl Phosphate.

MADE IN U.S.A
DISTRIBUTED BY:
ENERGIZER GROUP LTD
SWORD HOUSE, HP13 6DG
HIGH WYCOMBE, UK
www.bananaboat.co.uk

Manufactured by:
Accra Pac, Inc (dba KIK Custom Products)

PRINCIPAL DISPLAY PANEL

LOTION
UltraMist®
Banana
Boat®
Kids
Tear Free
ADVANCED UVA/UVB SPRAY SUN PROTECTION
SPF 50 UVA
AvoTriplex
High Protection TM
Sun-Tested, Sun-Proven TM
Fast & Even Coverage
Continuous Lotion Spray
Water Resistant
175 ml